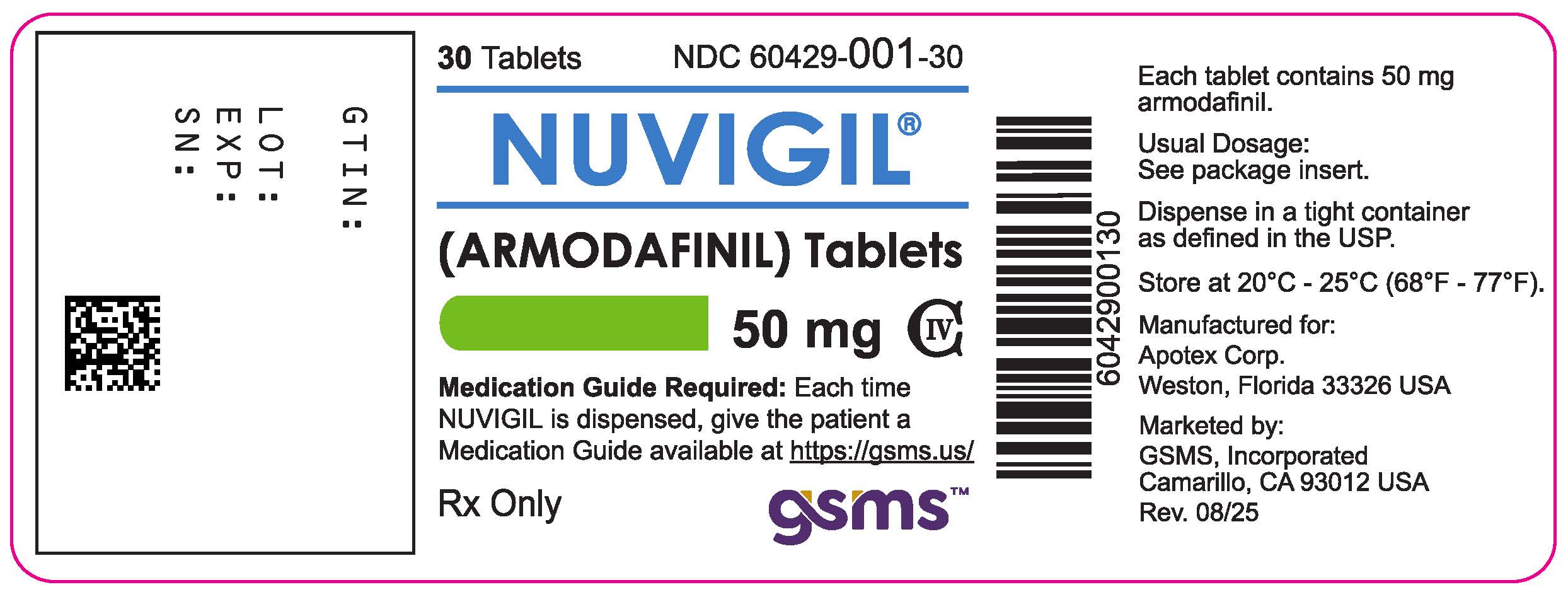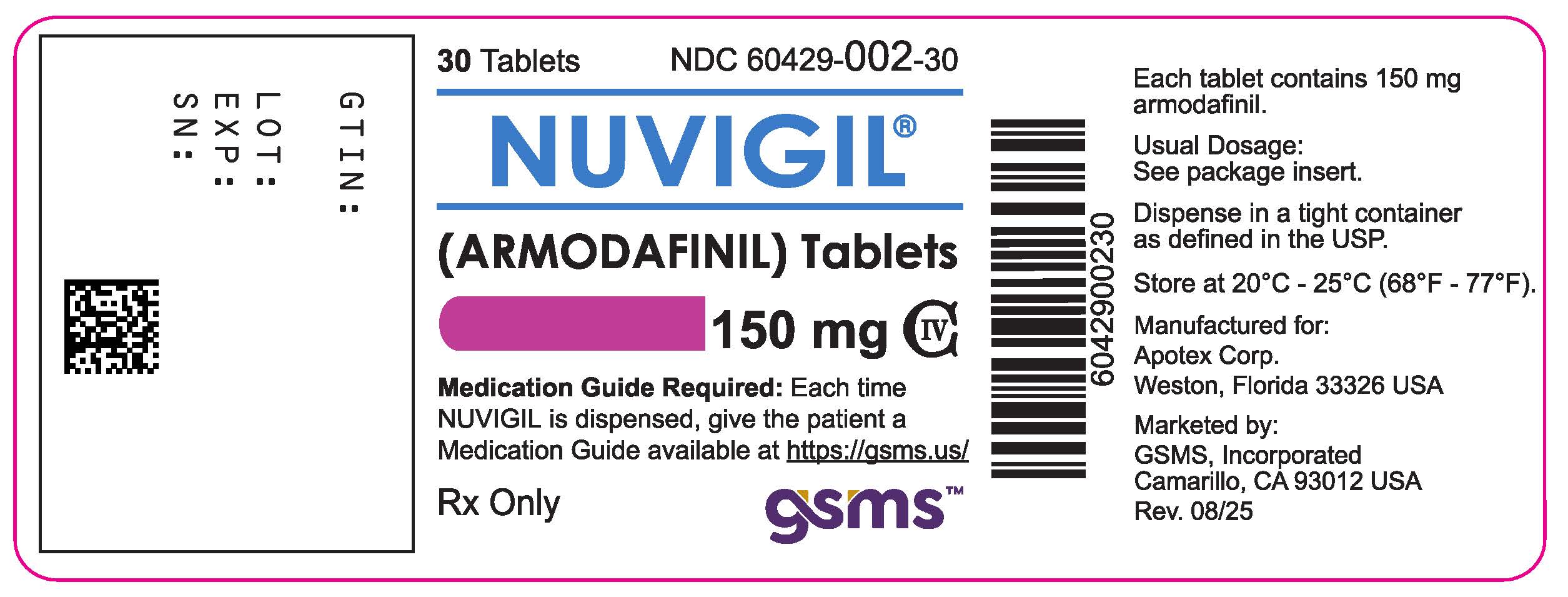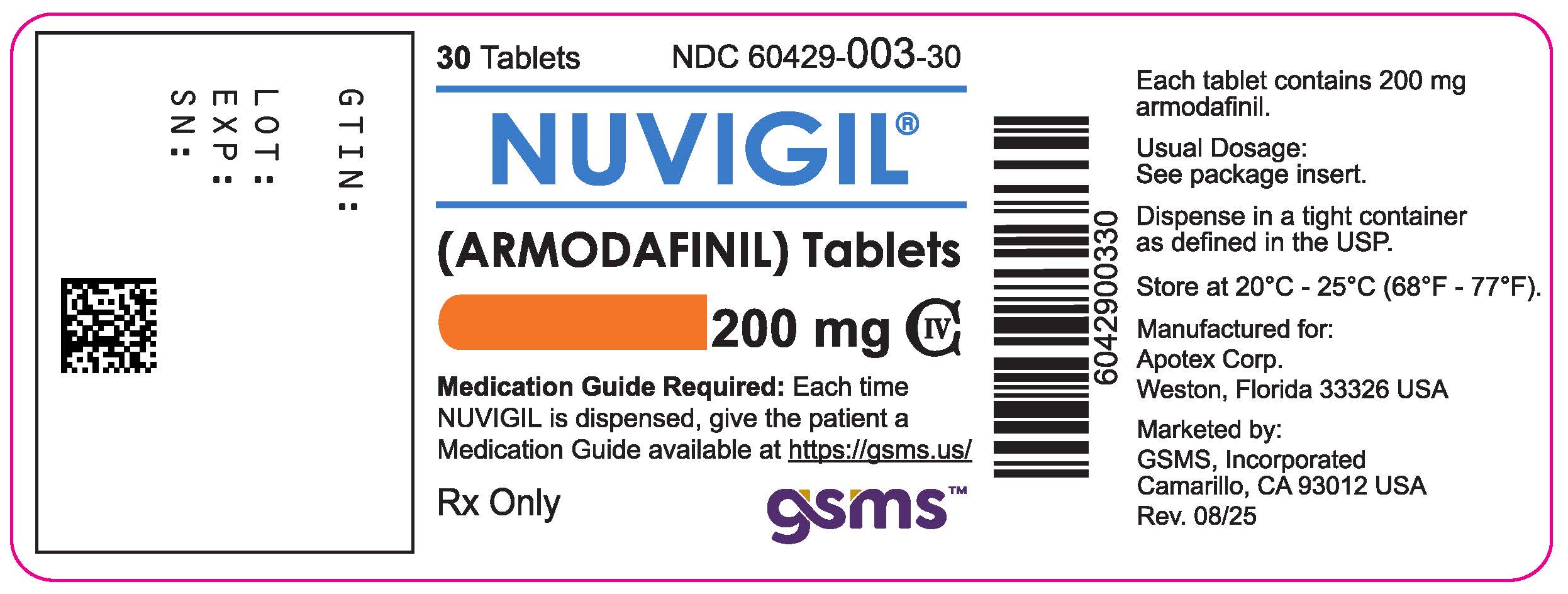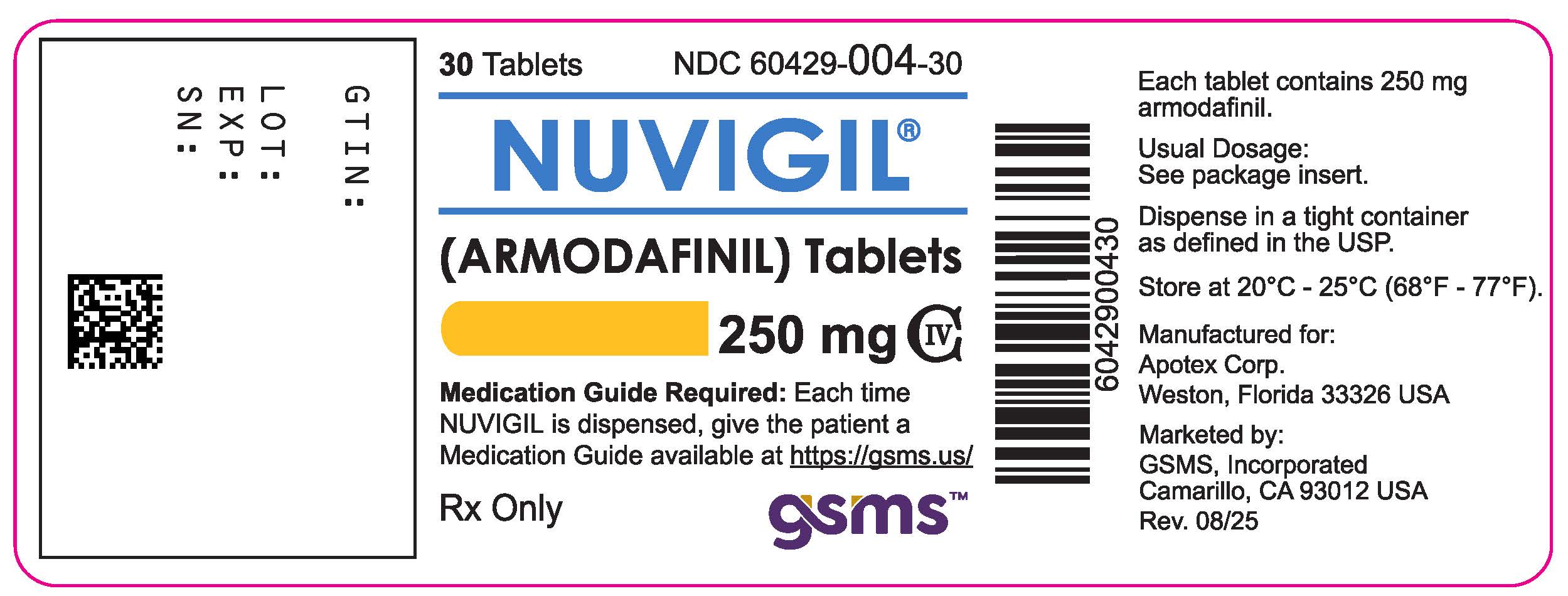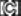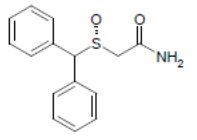 DRUG LABEL: Nuvigil
NDC: 60429-002 | Form: TABLET
Manufacturer: Golden State Medical Supply, Inc.
Category: prescription | Type: HUMAN PRESCRIPTION DRUG LABEL
Date: 20250902
DEA Schedule: CIV

ACTIVE INGREDIENTS: ARMODAFINIL 150 mg/1 1
INACTIVE INGREDIENTS: CROSCARMELLOSE SODIUM; LACTOSE MONOHYDRATE; MAGNESIUM STEARATE; MICROCRYSTALLINE CELLULOSE; POVIDONE K30; STARCH, CORN

HIGHLIGHTS OF PRESCRIBING INFORMATION

NUVIGIL ®(armodafinil) tablets. These highlights do not include all the information needed to use NUVIGIL safely and effectively. See full prescribing information for NUVIGIL.
NUVIGIL®(armodafinil) tablets, for oral use, C-IV
Initial U.S. Approval: 2007

1 INDICATIONS AND USAGE

NUVIGIL is indicated to improve wakefulness in adult patients with excessive sleepiness associated with obstructive sleep apnea (OSA), narcolepsy, or shift work disorder (SWD). (1)

Limitations of Use
In OSA, NUVIGIL is indicated to treat excessive sleepiness and not as treatment for the underlying obstruction.

2 DOSAGE AND ADMINISTRATION

The recommended dosage of NUVIGIL for each indication is as follows:

- OSA or Narcolepsy: 150 mg to 250 mg once a day in the morning. (2.1)
- SWD: 150 mg once a day, taken approximately one hour prior to start of the work shift. (2.2)
- Hepatic Impairment: reduced dose in patients with severe hepatic impairment. (2.3, 12.3)
- Geriatric Patients: consider lower dose. (2.4, 12.3)

3 DOSAGE FORMS AND STRENGTHS

Tablets: 50 mg, 150 mg, 200 mg, and 250 mg. (3)

4 CONTRAINDICATIONS

NUVIGIL is contraindicated in patients with known hypersensitivity to modafinil or armodafinil. (4)

5 WARNINGS AND PRECAUTIONS

- Serious Rash, including Stevens-Johnson Syndrome: discontinue NUVIGIL at the first sign of rash, unless the rash is clearly not drug-related. (5.1)
- DRESS/Multi-organ Hypersensitivity Reactions: if suspected, discontinue NUVIGIL. (5.2)
- Angioedema and Anaphylaxis Reactions: if suspected, discontinue NUVIGIL. (5.3)
- Persistent Sleepiness: assess patients frequently for degree of sleepiness and, if appropriate, advise patients to avoid driving or engaging in any other potentially dangerous activity. (5.4)
- Psychiatric Symptoms: use particular caution in treating patients with a history of psychosis, depression, or mania. Consider discontinuing NUVIGIL if psychiatric symptoms develop. (5.5)
- Known Cardiovascular Disease: consider increased monitoring. (5.7)

6 ADVERSE REACTIONS

Most common adverse reactions (≥5%): headache, nausea, dizziness, and insomnia. (6.1)

To report SUSPECTED ADVERSE REACTIONS, contact Apotex Corp. at 1-800-706-5575 or FDA at 1-800-FDA-1088 or www.fda.gov/medwatch.

7 DRUG INTERACTIONS

- Steroidal contraceptives (e.g., ethinyl estradiol): use alternative or concomitant methods of contraception while taking NUVIGIL and for one month after discontinuation of NUVIGIL treatment. (7)
- Cyclosporine: blood concentrations of cyclosporine may be reduced. (7)
- CYP2C19 substrates, such as omeprazole, phenytoin, and diazepam: exposure of these medications may be increased. (7)

8 USE IN SPECIFIC POPULATIONS

Pregnancy: based on animal data, may cause fetal harm. (8.1)

FULL PRESCRIBING INFORMATION

1 INDICATIONS AND USAGE

NUVIGIL is indicated to improve wakefulness in adult patients with excessive sleepiness associated with obstructive sleep apnea (OSA), narcolepsy, or shift work disorder (SWD).

Limitations of Use

In OSA, NUVIGIL is indicated to treat excessive sleepiness and not as treatment for the underlying obstruction. If continuous positive airway pressure (CPAP) is the treatment of choice for a patient, a maximal effort to treat with CPAP for an adequate period of time should be made prior to initiating NUVIGIL for excessive sleepiness.

2 DOSAGE AND ADMINISTRATION

2.1 Dosage in Obstructive Sleep Apnea (OSA) and Narcolepsy

The recommended dosage of NUVIGIL for patients with OSA or narcolepsy is 150 mg to 250 mg taken orally once a day as a single dose in the morning.

In patients with OSA, doses up to 250 mg/day, given as a single dose, have been well tolerated, but there is no consistent evidence that these doses confer additional benefit beyond that of the 150 mg/day dose [see Clinical Pharmacology (12.3) and Clinical Studies (14.1, 14.2)].

2.2 Dosage in Shift Work Disorder (SWD)

The recommended dosage of NUVIGIL for patients with SWD is 150 mg taken orally once a day as a single dose approximately 1 hour prior to the start of their work shift.

2.3 Dosage Modification in Patients with Severe Hepatic Impairment

In patients with severe hepatic impairment, the dosage of NUVIGIL should be reduced [see Use in Specific Populations (8.6) and Clinical Pharmacology (12.3)].

2.4 Use in Geriatric Patients

Consideration should be given to the use of lower doses and close monitoring in geriatric patients [see Use in Specific Populations (8.5)].

3 DOSAGE FORMS AND STRENGTHS

- 50 mg – round, white to off-white tablet with on one side and "205" on the other
- 150 mg – oval, white to off-white tablet with on one side and "215" on the other
- 200 mg – rounded, rectangular, white to off-white tablet with on one side and "220" on the other
- 250 mg – oval, white to off-white tablet with on one side and "225" on the other

4 CONTRAINDICATIONS

NUVIGIL is contraindicated in patients with known hypersensitivity to modafinil or armodafinil or its inactive ingredients [see Warnings and Precautions (5.1, 5.2, 5.3)] .

5 WARNINGS AND PRECAUTIONS

5.1 Serious Dermatologic Reactions, including Stevens-Johnson Syndrome and Toxic Epidermal Necrosis

Serious rash requiring hospitalization and discontinuation of treatment has been reported in association with the use of NUVIGIL (armodafinil) or modafinil (the racemic mixture of S- and R-enantiomers).

NUVIGIL has not been studied in pediatric patients in any setting and is not approved for use in pediatric patients for any indication.

In clinical trials of modafinil, the incidence of rash resulting in discontinuation was approximately 0.8% (13 per 1,585) in pediatric patients (age <17 years); these rashes included 1 case of possible Stevens-Johnson syndrome (SJS) and 1 case of apparent multi-organ hypersensitivity reaction/ Drug Rash with Eosinophilia and Systemic Symptoms (DRESS) [see Warnings and Precautions (5.2)]. Several of the cases were associated with fever and other abnormalities (e.g., vomiting, leukopenia). The median time to rash that resulted in discontinuation was 13 days. No such cases were observed among 380 pediatric patients who received placebo.

Skin and mouth sores, blistering, and ulceration have been reported with modafinil and NUVIGIL in the postmarketing setting. Recurrence of signs and symptoms of serious dermatologic reactions following rechallenge has been reported in some cases.

Rare cases of serious or life-threatening rash, including SJS and toxic epidermal necrolysis (TEN), have been reported in adults and children in worldwide postmarketing experience with modafinil and NUVIGIL.

There are no factors, including duration of therapy, that are known to predict the risk of occurrence or the severity of rash associated with modafinil or NUVIGIL. In cases where the time to onset was reported, serious rash occurred 1 day to 2 months after initiation of treatment, but isolated cases of serious dermatologic reactions have been reported with symptoms beginning after prolonged treatment (e.g., 3 months).

Although benign rashes also occur with NUVIGIL, it is not possible to reliably predict which rashes will prove to be serious. Accordingly, NUVIGIL should be discontinued at the first sign of rash, skin or mouth sores, or blistering or ulceration, unless the rash is clearly not drug-related. Discontinuation of treatment may not prevent a rash from becoming life-threatening or permanently disabling or disfiguring.

5.2 Drug Reaction with Eosinophilia and System Symptoms (DRESS)/Multiorgan Hypersensitivity

DRESS, also known as multi-organ hypersensitivity, has been reported with NUVIGIL. DRESS typically, although not exclusively, presents with fever, rash, lymphadenopathy, and/or facial swelling, in association with other organ system involvement, such as hepatitis, nephritis, hematologic abnormalities, myocarditis, or myositis, sometimes resembling an acute viral infection. Eosinophilia is often present. This disorder is variable in its expression, and other organ systems not noted here may be involved. It is important to note that early manifestations of hypersensitivity (e.g., fever, lymphadenopathy) may be present even though rash is not evident.

One fatal case of DRESS that occurred in close temporal association (3 weeks) with the initiation of NUVIGIL treatment has been reported in the postmarketing setting. In addition, multi-organ hypersensitivity reactions, including at least one fatality in postmarketing experience, have occurred in close temporal association (median time to detection 13 days; range 4-33) to the initiation of modafinil. Although there have been a limited number of reports, multi-organ hypersensitivity reactions may result in hospitalization or be life-threatening.

If a multi-organ hypersensitivity reaction is suspected, NUVIGIL should be discontinued. Although there are no case reports to indicate cross-sensitivity with other drugs that produce this syndrome, the experience with drugs associated with multi-organ hypersensitivity would indicate this to be a possibility.

5.3 Angioedema and Anaphylaxis Reactions

Angioedema and hypersensitivity (with rash, dysphagia, and bronchospasm), were observed with NUVIGIL. Patients should be advised to discontinue therapy and immediately report to their physician any signs or symptoms suggesting angioedema or anaphylaxis (e.g., swelling of face, eyes, lips, tongue or larynx; difficulty in swallowing or breathing; hoarseness).

5.4 Persistent Sleepiness

Patients with abnormal levels of sleepiness who take NUVIGIL should be advised that their level of wakefulness may not return to normal. Patients with excessive sleepiness, including those taking NUVIGIL, should be frequently reassessed for their degree of sleepiness and, if appropriate, advised to avoid driving or any other potentially dangerous activity. Prescribers should also be aware that patients may not acknowledge sleepiness or drowsiness until directly questioned about drowsiness or sleepiness during specific activities.

5.5 Psychiatric Symptoms

In pre-approval narcolepsy, OSA and SWD controlled trials of NUVIGIL, anxiety, agitation, nervousness, and irritability were reasons for treatment discontinuation more often in patients on NUVIGIL compared to placebo (NUVIGIL 1.2% and placebo 0.3%). Depression was also a reason for treatment discontinuation more often in patients on NUVIGIL compared to placebo (NUVIGIL 0.6% and placebo 0.2%). Cases of suicidal ideation were observed in clinical trials.

Caution should be exercised when NUVIGIL is given to patients with a history of psychosis, depression, or mania. If psychiatric symptoms develop in association with NUVIGIL administration, consider discontinuing NUVIGIL.

Psychiatric adverse reactions have been reported in patients treated with modafinil. Modafinil and NUVIGIL (armodafinil) are very closely related. Therefore, the incidence and type of psychiatric symptoms associated with NUVIGIL are expected to be similar to the incidence and type of these events with modafinil.

Postmarketing adverse reactions associated with the use of NUVIGIL, some of which have resulted in hospitalization, have included mania, delusions, hallucinations, suicidal ideation, and aggression. Many, but not all, patients who developed psychiatric adverse reactions had a prior psychiatric history. In these cases, reported NUVIGIL total daily doses ranged from 50 mg to 450 mg, which includes doses below and above the recommended dosages.

5.6 Effects on Ability to Drive and Use Machinery

Although NUVIGIL has not been shown to produce functional impairment, any drug affecting the central nervous system (CNS) may alter judgment, thinking or motor skills. Patients should be cautioned about operating an automobile or other hazardous machinery until it is reasonably certain that NUVIGIL therapy will not adversely affect their ability to engage in such activities.

5.7 Cardiovascular Events

In clinical studies of modafinil, cardiovascular adverse reactions, including chest pain, palpitations, dyspnea and transient ischemic T-wave changes on ECG were observed in three subjects in association with mitral valve prolapse or left ventricular hypertrophy. It is recommended that NUVIGIL tablets not be used in patients with a history of left ventricular hypertrophy or in patients with mitral valve prolapse who have experienced the mitral valve prolapse syndrome when previously receiving CNS stimulants. Findings suggestive of mitral valve prolapse syndrome include but are not limited to ischemic ECG changes, chest pain, or arrhythmia. If new onset of any of these findings occurs, consider cardiac evaluation.

Blood pressure monitoring in short term (≤ 3 months) pre-approval controlled trials of OSA, SWD, and narcolepsy showed small average increases in mean systolic and diastolic blood pressure in patients receiving NUVIGIL as compared to placebo (1.2 to 4.3 mmHg in the various experimental groups). There was also a slightly greater proportion of patients on NUVIGIL requiring new or increased use of antihypertensive medications (2.9%) compared to patients on placebo (1.8%). There was a small, but consistent, average increase in pulse rate over placebo in pre-approval controlled trials. This increase varied from 0.9 to 3.5 BPM. Increased monitoring of heart rate and blood pressure may be appropriate in patients on NUVIGIL. Caution should be exercised when prescribing NUVIGIL to patients with known cardiovascular disease.

6 ADVERSE REACTIONS

The following serious adverse reactions are described below and elsewhere in the labeling:

- Serious Dermatologic Reactions [see Warnings and Precautions (5.1)]
- Drug Reaction with Eosinophilia and System Symptoms (DRESS)/Multiorgan Hypersensitivity [see Warnings and Precautions (5.2)]
- Angioedema and Anaphylaxis Reactions [see Warnings and Precautions (5.3)]
- Persistent Sleepiness [see Warnings and Precautions (5.4)]
- Psychiatric Symptoms [see Warnings and Precautions (5.5)]
- Effects on Ability to Drive and Use Machinery [see Warnings and Precautions (5.6)]
- Cardiovascular Events [see Warnings and Precautions (5.7)]

6.1 Clinical Trials Experience

Because clinical trials are conducted under widely varying conditions, adverse reaction rates observed in the clinical trials of a drug cannot be directly compared to rates in the clinical trials of another drug and may not reflect the rates observed in practice.

NUVIGIL has been evaluated for safety in over 1,100 patients with excessive sleepiness associated with OSA, SWD, and narcolepsy.

Most Common Adverse Reactions

In the placebo-controlled clinical trials, the most common adverse reactions (≥5%) associated with the use of NUVIGIL more frequently than in placebo-treated patients were headache, nausea, dizziness, and insomnia. The adverse reaction profile was similar across the studies.

Table 1presents the adverse reactions that occurred at a rate of 1% or more and were more frequent in NUVIGIL-treated patients than in placebo-treated patients in the placebo-controlled clinical trials.

Table 1: Adverse Reactions in Pooled Placebo-Controlled Clinical Trials* in OSA, Narcolepsy, and SWD with NUVIGIL (150 mg and 250 mg)
 | NUVIGIL (%) N=645 | Placebo (%) N=445
Headache | 17 | 9
Nausea | 7 | 3
Dizziness | 5 | 2
Insomnia | 5 | 1
Anxiety | 4 | 1
Diarrhea | 4 | 2
Dry Mouth | 4 | 1
Depression | 2 | 0
Dyspepsia | 2 | 0
Fatigue | 2 | 1
Palpitations | 2 | 1
Rash | 2 | 0
Upper Abdominal Pain | 2 | 1
Agitation | 1 | 0
Anorexia | 1 | 0
Constipation | 1 | 0
Contact Dermatitis | 1 | 0
Decreased Appetite | 1 | 0
Depressed Mood | 1 | 0
Disturbance In Attention | 1 | 0
Dyspnea | 1 | 0
Hyperhydrosis | 1 | 0
Increased Gamma-Glutamyltransferase | 1 | 0
Increased Heart Rate | 1 | 0
Influenza-Like Illness | 1 | 0
Loose Stools | 1 | 0
Migraine | 1 | 0
Nervousness | 1 | 0
Pain | 1 | 0
Paresthesia | 1 | 0
Polyuria | 1 | 0
Pyrexia | 1 | 0
Seasonal Allergy | 1 | 0
Thirst | 1 | 0
Tremor | 1 | 0
Vomiting | 1 | 0
* Adverse reactions that occurred in >1% of NUVIGIL-treated patients and greater incidence than that of placebo.

Dose-Dependent Adverse Reactions

In the placebo-controlled clinical trials which compared doses of 150 mg/day and 250 mg/day of NUVIGIL and placebo, the following adverse reactions were dose-related: headache, rash, depression, dry mouth, insomnia, and nausea. See Table 2for additional information.

Table 2: Dose-Dependent Adverse Reactions in Pooled Placebo-Controlled Clinical Trials in OSA, Narcolepsy and SWD
 | NUVIGIL 250 mg (%) N=198 | NUVIGIL 150 mg (%) N=447 | NUVIGIL Combined (%) N=645 | Placebo (%) N=445
Headache | 23 | 14 | 17 | 9
Nausea | 9 | 6 | 7 | 3
Insomnia | 6 | 4 | 5 | 1
Dry Mouth | 7 | 2 | 4 | <1
Rash | 4 | 1 | 2 | <1
Depression | 3 | 1 | 2 | <1

Adverse Reactions Resulting in Discontinuation of Treatment

In placebo-controlled clinical trials, 44 of the 645 patients (7%) who received NUVIGIL discontinued due to an adverse reaction compared to 16 of the 445 (4%) of patients that received placebo. The most frequent reason for discontinuation was headache (1%).

Laboratory Abnormalities

Clinical chemistry, hematology, and urinalysis parameters were monitored in the studies. Mean plasma levels of gamma glutamyltransferase (GGT) and alkaline phosphatase (AP) were found to be higher following administration of NUVIGIL, but not placebo. Few patients, however, had GGT or AP elevations outside of the normal range. No differences were apparent in alanine aminotransferase (ALT), aspartate aminotransferase (AST), total protein, albumin, or total bilirubin, although there were rare cases of isolated elevations of AST and/or ALT. A single case of mild pancytopenia was observed after 35 days of treatment and resolved with drug discontinuation. A small mean decrease from baseline in serum uric acid compared to placebo was seen in clinical trials. The clinical significance of this finding is unknown.

6.2 Postmarketing Experience

The following adverse reactions have been identified during post approval use of NUVIGIL. Because these reactions are reported voluntarily from a population of uncertain size, it is not always possible to reliably estimate their frequency or establish a causal relationship to drug exposure.

Gastrointestinal Disorders:Mouth Sores (including mouth blistering and ulceration)

7 DRUG INTERACTIONS

Effects of NUVIGIL on CYP3A4/5 Substrates

The clearance of drugs that are substrates for CYP3A4/5 (e.g., steroidal contraceptives, cyclosporine, midazolam, and triazolam) may be increased by NUVIGIL via induction of metabolic enzymes, which results in lower systemic exposure. Dosage adjustment of these drugs should be considered when these drugs are used concomitantly with NUVIGIL [see Clinical Pharmacology (12.3)].

The effectiveness of steroidal contraceptives may be reduced when used with NUVIGIL and for one month after discontinuation of therapy. Alternative or concomitant methods of contraception are recommended for patients taking steroidal contraceptives (e.g., ethinyl estradiol) when treated concomitantly with NUVIGIL and for one month after discontinuation of NUVIGIL treatment.

Blood levels of cyclosporine may be reduced when used with NUVIGIL. Monitoring of circulating cyclosporine concentrations and appropriate dosage adjustment for cyclosporine should be considered when used concomitantly with NUVIGIL.

Effects of NUVIGIL on CYP2C19 Substrates

Elimination of drugs that are substrates for CYP2C19 (e.g., phenytoin, diazepam, propranolol, omeprazole, and clomipramine) may be prolonged by NUVIGIL via inhibition of metabolic enzymes, with resultant higher systemic exposure. Dose reduction of these drugs may be required when these drugs are used concomitantly with NUVIGIL.

Warfarin

More frequent monitoring of prothrombin times/INR should be considered whenever NUVIGIL is coadministered with warfarin [see Clinical Pharmacology (12.3)].

Monoamine Oxidase (MAO) Inhibitors

Caution should be used when concomitantly administering MAO inhibitors and NUVIGIL.

8 USE IN SPECIFIC POPULATIONS

8.1 Pregnancy

Pregnancy Registry

There is a pregnancy exposure registry that monitors pregnancy outcomes in women exposed to NUVIGIL during pregnancy. Healthcare providers are encouraged to register pregnant patients, or pregnant women may enroll themselves in the registry by calling 1-866-404-4106.

Risk Summary

Limited available data on armodafinil use in pregnant women are insufficient to inform a drug associated risk of adverse pregnancy outcomes. Intrauterine growth restriction and spontaneous abortion have been reported in association with armodafinil and modafinil. Although the pharmacology of armodafinil is not identical to that of the sympathomimetic amines, armodafinil shares some pharmacologic properties with this class [see Clinical Pharmacology (12.1)] . Some sympathomimetics have been associated with intrauterine growth restriction and spontaneous abortions.

In animal reproduction studies of armodafinil (R-modafinil) and modafinil (a mixture of R- and S-modafinil) conducted in pregnant rats (armodafinil, modafinil) and rabbits (modafinil) during organogenesis, evidence of developmental toxicity (increased embryofetal and offspring mortality, decreased fetal growth) was observed at clinically relevant plasma exposures.

All pregnancies have a background risk of birth defects, loss, or other adverse outcomes. The estimated background risk of major birth defects and miscarriage for the indicated populations is unknown. In the U.S. general population, the estimated background risk of major birth defects and miscarriage in clinically recognized pregnancies is 2-4% and 15-20%, respectively.

Data

Animal Data

Oral administration of armodafinil (60, 200, or 600 mg/kg/day) to pregnant rats throughout organogenesis resulted in decreased fetal body weight and increased incidences of fetal variations indicative of growth delay at the highest dose, which was also maternally toxic. The highest no-effect dose for embryofetal developmental toxicity in rat (200 mg/kg/day) was associated with a plasma armodafinil exposure (AUC) less than that in humans at the maximum recommended human dose (MRHD) of NUVIGIL (250 mg/day).

Modafinil (50, 100, or 200 mg/kg/day) administered orally to pregnant rats throughout organogenesis produced an increase in resorptions and an increased incidence of fetal variations at the highest dose tested. The higher no-effect dose for embryofetal developmental toxicity (100 mg/kg/day) was associated with a plasma armodafinil AUC less than that in humans at the MRHD of NUVIGIL. However, in a subsequent rat study of up to 480 mg/kg/day of modafinil, no adverse effects on embryofetal development were observed.

In a study in which modafinil (45, 90, or 180 mg/kg/day) was orally administered to pregnant rabbits during organogenesis, embryofetal death was increased at the highest dose. The highest no-effect dose for developmental toxicity (100 mg/kg/day) was associated with a plasma armodafinil AUC less than that in humans at the MRHD of NUVIGIL.

Modafinil administration to rats throughout gestation and lactation at oral doses of up to 200 mg/kg/day resulted in decreased viability in the offspring at doses greater than 20 mg/kg/day, a dose resulting in a plasma armodafinil AUC less than that in humans at the MRHD of NUVIGIL. No effects on postnatal developmental and neurobehavioral parameters were observed in surviving offspring.

8.2 Lactation

Risk Summary

There are no data on the presence of armodafinil or its metabolites in human milk, the effects on the breastfed infant, or the effect of this drug on milk production. Modafinil was present in rat milk when animals were dosed during the lactation period. The developmental and health benefits of breastfeeding should be considered along with the mother’s clinical need for armodafinil and any potential adverse effects on the breastfed child from armodafinil or from the underlying maternal condition.

8.3 Females and Males of Reproductive Potential

The effectiveness of hormonal contraceptives may be reduced when used with NUVIGIL and for one month after discontinuation of therapy. Advise women who are using a hormonal method of contraception to use an additional barrier method or an alternative non-hormonal method of contraception during treatment with NUVIGIL and for one month after discontinuation of NUVIGIL treatment [see Drug Interactions (7) and Clinical Pharmacology (12.3)] .

8.4 Pediatric Use

Safety and effectiveness in pediatric patients have not been established. Serious rash has been seen in pediatric patients receiving modafinil [see Warnings and Precautions (5.1)].

8.5 Geriatric Use

In elderly patients, elimination of armodafinil and its metabolites may be reduced as a consequence of aging. Therefore, consideration should be given to the use of lower doses and close monitoring in this population [see Dosage and Administration (2.4) and Clinical Pharmacology (12.3)].

8.6 Hepatic Impairment

The dosage of NUVIGIL should be reduced in patients with severe hepatic impairment [see Dosage and Administration (2.3) and Clinical Pharmacology (12.3)] .

9 DRUG ABUSE AND DEPENDENCE

9.1 Controlled Substance

NUVIGIL contains armodafinil, a Schedule IV controlled substance.

9.2 Abuse

Abuse of NUVIGIL has been reported in patients treated with NUVIGIL. Patterns of abuse have included euphoric mood and use of increasingly large doses or recurrent use of NUVIGIL for a desired effect. Drug diversion has also been noted. During the postmarketing period, misuse of NUVIGIL has been observed (e.g., taking NUVIGIL against a physician’s advice, and obtaining NUVIGIL from multiple physicians).

Abuse of armodafinil, the active ingredient of NUVIGIL, poses a risk of overdosage similar to that seen for modafinil, which may lead to tachycardia, insomnia, agitation, dizziness, anxiety, nausea, headache, dystonia, tremor, chest pain, hypertension, seizures, delirium, or hallucinations. Other signs and symptoms of CNS stimulant abuse include tachypnea, sweating, dilated pupils, hyperactivity, restlessness, decreased appetite, loss of coordination, flushed skin, vomiting, and abdominal pain.

In humans, modafinil produces psychoactive and euphoric effects, alterations in mood, perception, thinking and feelings, typical of other CNS stimulants. In in vitro binding studies, modafinil binds to the dopamine reuptake site and causes an increase in extracellular dopamine, but no increase in dopamine release. Modafinil is reinforcing, as evidenced by its self-administration in monkeys previously trained to self-administer cocaine. In some studies, modafinil was also partially discriminated as stimulant-like.

Physicians should follow patients closely, especially those with a history of drug and/or stimulant (e.g., methylphenidate, amphetamine, or cocaine) abuse. Patients should be observed for signs of misuse or abuse (e.g., incrementation of doses or drug-seeking behavior).

The abuse potential of modafinil (200, 400, and 800 mg) was assessed relative to methylphenidate (45 and 90 mg) in an inpatient study in individuals experienced with drugs of abuse. Results from this clinical study demonstrated that modafinil produced psychoactive and euphoric effects and feelings consistent with other scheduled CNS stimulants (methylphenidate).

9.3 Dependence

Physical dependence is a state that develops as a result of physiological adaptation in response to repeated drug use, manifested by withdrawal signs and symptoms after abrupt discontinuation or a significant dose reduction of a drug.

Physical dependence can occur in patients treated with NUVIGIL. Abrupt cessation or dose reduction following chronic use can result in withdrawal symptoms, including shaking, sweating, chills, nausea, vomiting, confusion, aggression, and atrial fibrillation.

Drug withdrawal convulsions, suicidality, fatigue, insomnia, aches, depression and headache have also been observed during the postmarketing period. Also, abrupt withdrawal has caused deterioration of psychiatric symptoms such as depression.

Tolerance is a physiological state characterized by a reduced response to a drug after repeated administration (i.e., a higher dose of a drug is required to produce the same effect that was once obtained at a lower dose).

Multiple cases of development of tolerance to NUVIGIL have been reported during the postmarketing period.

10 OVERDOSAGE

Fatal overdoses involving modafinil alone or involving NUVIGIL or modafinil in combination with other drugs have been reported in the postmarketing setting. Symptoms most often accompanying NUVIGIL or modafinil overdose, alone or in combination with other drugs, have included anxiety, dyspnea, insomnia; central nervous system symptoms such as restlessness, disorientation, confusion, excitation and hallucination; digestive changes such as nausea and diarrhea; and cardiovascular changes such as tachycardia, bradycardia, hypertension, and chest pain.

No specific antidote exists for the toxic effects of a NUVIGIL overdose. Such overdoses should be managed with primarily supportive care, including cardiovascular monitoring.

11 DESCRIPTION

NUVIGIL (armodafinil) is a wakefulness-promoting agent for oral administration. Armodafinil is the R-enantiomer of modafinil which is a 1:1 mixture of the R- and S-enantiomers. The chemical name for armodafinil is 2-[(R)-(diphenylmethyl)sulfinyl]acetamide. The molecular formula is C15H15NO2S and the molecular weight is 273.35.

The chemical structure is:

Armodafinil is a white to off-white, crystalline powder that is slightly soluble in water, sparingly soluble in acetone, and soluble in methanol.

NUVIGIL tablets contain 50, 150, 200 or 250 mg of armodafinil and the following inactive ingredients: croscarmellose sodium, lactose monohydrate, magnesium stearate, microcrystalline cellulose, povidone, and pregelatinized starch.

12 CLINICAL PHARMACOLOGY

12.1 Mechanism of Action

The mechanism(s) through which armodafinil promotes wakefulness is unknown. Armodafinil (R-modafinil) has pharmacological properties similar to those of modafinil (a mixture of R- and S-modafinil), to the extent tested in animal and in vitro studies. The R- and S-enantiomers have similar pharmacological actions in animals.

Armodafinil and modafinil have wake-promoting actions similar to sympathomimetic agents including amphetamine and methylphenidate, although their pharmacologic profile is not identical to that of the sympathomimetic amines.

Modafinil-induced wakefulness can be attenuated by the α1-adrenergic receptor antagonist, prazosin; however, modafinil is inactive in other in vitro assay systems known to be responsive to α-adrenergic agonists such as the rat vas deferens preparation.

Armodafinil is an indirect dopamine receptor agonist; both armodafinil and modafinil bind in vitro to the dopamine transporter and inhibit dopamine reuptake. For modafinil, this activity has been associated in vivo with increased extracellular dopamine levels in some brain regions of animals. In genetically engineered mice lacking the dopamine transporter (DAT), modafinil lacked wake-promoting activity, suggesting that this activity was DAT-dependent. However, the wake-promoting effects of modafinil, unlike those of amphetamine, were not antagonized by the dopamine receptor antagonist haloperidol in rats. In addition, alpha-methyl-p-tyrosine, a dopamine synthesis inhibitor, blocks the action of amphetamine, but does not block locomotor activity induced by modafinil.

In addition to its wake-promoting effects and ability to increase locomotor activity in animals, modafinil produces psychoactive and euphoric effects, alterations in mood, perception, thinking, and feelings typical of other CNS stimulants in humans. Modafinil has reinforcing properties, as evidenced by its self-administration in monkeys previously trained to self-administer cocaine; modafinil was also partially discriminated as stimulant-like.

Based on nonclinical studies, two major metabolites, acid and sulfone, of modafinil or armodafinil, do not appear to contribute to the CNS-activating properties of the parent compounds.

12.3 Pharmacokinetics

Armodafinil exhibits linear time-independent kinetics following single and multiple oral dose administration. Increase in systemic exposure is proportional over the dose range of 50 to 400 mg. No time-dependent change in kinetics was observed through 12 weeks of dosing. Apparent steady state for armodafinil was reached within 7 days of dosing. At steady state, the systemic exposure for armodafinil is 1.8 times the exposure observed after a single dose. The concentration-time profiles of the R-enantiomer following administration of a single-dose of 50 mg NUVIGIL or 100 mg PROVIGIL (modafinil, a 1:1 mixture of R- and S-enantiomers) are nearly superimposable. However, the Cmaxand AUC0-∞, of armodafinil at steady-state were approximately 37% and 70% higher, respectively, following administration of 200 mg NUVIGIL than the corresponding values of modafinil following administration of 200 mg PROVIGIL due to the more rapid clearance of the S-enantiomer (elimination half-life approximately 4 hours) as compared to the R-enantiomer.

Absorption

NUVIGIL is readily absorbed after oral administration. The absolute oral bioavailability was not determined due to the aqueous insolubility of armodafinil, which precluded intravenous administration. Peak plasma concentrations are attained at approximately 2 hours in the fasted state. Food effect on the overall bioavailability of NUVIGIL is considered minimal; however, time to reach peak concentration (tmax) may be delayed by approximately 2-4 hours in the fed state. Since the delay in tmaxis also associated with elevated plasma concentrations later in time, food can potentially affect the onset and time course of pharmacologic action for NUVIGIL.

Distribution

NUVIGIL has an apparent volume of distribution of approximately 42 L. Data specific to armodafinil protein binding are not available. However, modafinil is moderately bound to plasma protein (approximately 60%), mainly to albumin. The potential for interactions of NUVIGIL with highly protein‑bound drugs is considered to be minimal.

Elimination

After oral administration of NUVIGIL, armodafinil exhibits an apparent monoexponential decline from the peak plasma concentration. The apparent terminal t½is approximately 15 hours. The oral clearance of NUVIGIL is approximately 33 mL/min.

Metabolism

In vitro and in vivo data show that armodafinil undergoes hydrolytic deamidation, S-oxidation, and aromatic ring hydroxylation, with subsequent glucuronide conjugation of the hydroxylated products. Amide hydrolysis is the single most prominent metabolic pathway, with sulfone formation by cytochrome P450 (CYP) 3A4/5 being next in importance. The other oxidative products are formed too slowly in vitro to enable identification of the enzyme(s) responsible. Only two metabolites reach appreciable concentrations in plasma (i.e., R-modafinil acid and modafinil sulfone).

Excretion

Data specific to NUVIGIL disposition are not available. However, modafinil is mainly eliminated via metabolism, predominantly in the liver, with less than 10% of the parent compound excreted in the urine. A total of 81% of the administered radioactivity was recovered in 11 days post-dose, predominantly in the urine (80% vs. 1.0% in the feces).

Specific Populations

Age

In a clinical study, systemic exposure of armodafinil was approximately 15% higher in elderly subjects (≥65 years of age, N=24), corresponding to approximately 12% lower oral clearance (CL/F), as compared to young subjects (18-45 years of age, N=25). Systemic exposure of armodafinil acid (metabolite) was approximately 61% and 73% greater for Cmaxand AUC0-τ, respectively, compared to young subjects. Systemic exposure of the sulfone metabolite was approximately 20% lower for elderly subjects compared with young subjects. A subgroup analysis of elderly subjects demonstrated elderly subjects ≥75 and 65-74 years of age had approximately 21% and 9% lower oral clearance, respectively, compared to young subjects. Systemic exposure was approximately 10% greater in subjects 65-74 years of age (N=17) and 27% greater in subjects ≥75 years of age (N=7), respectively, when compared to young subjects. The change is considered not likely to be clinically significant for elderly patients, however, because some elderly patients have greater exposure to armodafinil, consideration should be given to the use of lower doses.

Sex

Population pharmacokinetic analysis suggests no gender effect on the pharmacokinetics of armodafinil.

Ethnicity

The influence of race/ethnicity on the pharmacokinetics of armodafinil has not been studied.

Hepatic Impairment

The pharmacokinetics and metabolism of modafinil were examined in patients with cirrhosis of the liver (6 men and 3 women). Three patients had stage B or B+ cirrhosis and 6 patients had stage C or C+ cirrhosis (per the Child-Pugh score criteria). Clinically 8 of 9 patients were icteric and all had ascites. In these patients, the oral clearance of modafinil was decreased by about 60% and the steady state concentration was doubled compared to normal patients [see Dosage and Administration (2.3) and Use in Specific Populations (8.6)] .

Renal Impairment

In a single dose 200 mg modafinil study, severe chronic renal failure (creatinine clearance ≤20 mL/min) did not significantly influence the pharmacokinetics of modafinil, but exposure to modafinil acid (metabolite) was increased 9-fold.

Drug Interactions

In vitro data demonstrated that armodafinil weakly induces CYP1A2 and possibly CYP3A activities in a concentration-related manner and that CYP2C19 activity is reversibly inhibited by armodafinil. Other CYP activities did not appear to be affected by armodafinil. An in vitro study demonstrated that armodafinil is a substrate of P-glycoprotein.

Potential Interactions with Drugs That Inhibit, Induce, or Are Metabolized by Cytochrome P450 Isoenzymes and Other Hepatic Enzymes

The existence of multiple pathways for armodafinil metabolism, as well as the fact that a non-CYP-related pathway is the most rapid in metabolizing armodafinil, suggest that there is a low probability of substantive effects on the overall pharmacokinetic profile of NUVIGIL due to CYP inhibition by concomitant medications. However, due to the partial involvement of CYP3A enzymes in the metabolic elimination of armodafinil, coadministration of potent inducers of CYP3A4/5 (e.g., carbamazepine, phenobarbital, rifampin) or inhibitors of CYP3A4/5 (e.g., ketoconazole, erythromycin) could alter the plasma concentrations of armodafinil.

The Potential of NUVIGIL to Alter the Metabolism of Other Drugs by Enzyme Induction or Inhibition

- Drugs Metabolized by CYP3A4/5
  In vitro data demonstrated that armodafinil is a weak inducer of CYP3A activity in a concentration-related manner. In a clinical study, concomitant administration of NUVIGIL 250 mg resulted in a reduction in systemic exposure to midazolam by 32% after a single oral dose (5 mg) and 17% after a single intravenous dose (2 mg). Therefore, the blood levels and effectiveness of drugs that are substrates for CYP3A enzymes (e.g., steroidal contraceptives, cyclosporine, midazolam, and triazolam) may be reduced after initiation of concomitant treatment with NUVIGIL [see Drug Interactions (7)] .
  In a separate clinical study, concomitant administration of NUVIGIL 250 mg with quetiapine (300 mg to 600 mg daily doses) resulted in a reduction in the mean systemic exposure of quetiapine by approximately 29%. No dose adjustment is required.
- Drugs Metabolized by CYP1A2
  In vitro data demonstrated that armodafinil is a weak inducer of CYP1A2 in a concentration-related manner. However, in a clinical study using caffeine as a probe substrate, no significant effect on CYP1A2 activity was observed.
- Drugs Metabolized by CYP2C19
  In vitro data demonstrated that armodafinil is a reversible inhibitor of CYP2C19 activity. In a clinical study, concomitant administration of NUVIGIL 400 mg resulted in a 40% increase in exposure to omeprazole after a single oral dose (40 mg), as a result of moderate inhibition of CYP2C19 activity [see Drug Interactions (7)] .
- Interactions with CNS Active Drugs
  Concomitant administration of NUVIGIL with quetiapine reduced the systemic exposure of quetiapine.
  Data specific to NUVIGIL drug-drug interaction potential with other CNS active drugs are not available. However, the following available drug-drug interaction information on modafinil should be applicable to NUVIGIL .
  Concomitant administration of modafinil with methylphenidate or dextroamphetamine produced no significant alterations on the pharmacokinetic profile of modafinil or either stimulant, even though the absorption of modafinil was delayed for approximately one hour.
  Concomitant modafinil or clomipramine did not alter the pharmacokinetic profile of either drug; however, one incident of increased levels of clomipramine and its active metabolite desmethylclomipramine was reported in a patient with narcolepsy during treatment with modafinil.
  Data specific to NUVIGIL or modafinil drug-drug interaction potential with monoamine oxidase (MAO) inhibitors are not available [see Drug Interactions (7)] .
- Interaction with P-Glycoprotein
  An in vitro study demonstrated that armodafinil is a substrate of P-glycoprotein. The impact of inhibition of P-glycoprotein is not known.
- Interactions with Other Drugs
  Data specific to NUVIGIL drug-drug interaction potential for additional other drugs are not available. However, the following available drug-drug interaction information on modafinil should be applicable to NUVIGIL.
  Warfarin: Concomitant administration of modafinil with warfarin did not produce significant changes in the pharmacokinetic profiles of R- and S-warfarin. However, since only a single dose of warfarin was tested in this study, an interaction cannot be ruled out [see Drug Interactions (7)] .

13 NONCLINICAL TOXICOLOGY

13.1 Carcinogenesis, Mutagenesis, Impairment of Fertility

Carcinogenesis
In a mouse carcinogenicity study, armodafinil (R-modafinil) was administered at oral doses of up to 300 mg/kg/day in males and 100 mg/kg/day in females for approximately two years, no tumorigenic effects were observed.

In a rat carcinogenicity study modafinil (a mixture of R- and S-modafinil) was administered at oral doses of up to 60 mg/kg/day for two years; no tumorigenic effects were observed.

At the highest doses studied in mouse and rat, the plasma armodafinil exposures (AUC) were less than that in humans at the MRHD of NUVIGIL (250 mg/day).

Mutagenesis

Armodafinil was negative in an in vitro bacterial reverse mutation assay and in an in vitro chromosomal aberration assay in human lymphocytes.

Modafinil was negative in a series of in vitro (i.e., bacterial reverse mutation, mouse lymphoma tk, chromosomal aberration in human lymphocytes, cell transformation in BALB/3T3 mouse embryo cells) or in vivo (mouse bone marrow micronucleus) assays.

Impairment of Fertility

A fertility and early embryonic development (to implantation) study was not conducted with armodafinil alone.

Oral administration of modafinil (doses of up to 480 mg/kg/day) to male and female rats prior to and throughout mating, and continuing in females through day 7 of gestation produced an increase in the time to mate at the highest dose; no effects were observed on other fertility or reproductive parameters. The no-effect dose of 240 mg/kg/day was associated with a plasma armodafinil AUC less than that in humans at the MRHD of NUVIGIL.

14 CLINICAL STUDIES

14.1 Obstructive Sleep Apnea (OSA)

The effectiveness of NUVIGIL in improving wakefulness in patients with excessive sleepiness associated with OSA was established in two 12-week, multi-center, placebo-controlled, parallel-group, double-blind clinical studies of outpatients who met the criteria for OSA. The criteria include either: 1) excessive sleepiness or insomnia, plus frequent episodes of impaired breathing during sleep, and associated features such as loud snoring, morning headaches or dry mouth upon awakening; or 2) excessive sleepiness or insomnia; and polysomnography demonstrating one of the following: more than five obstructive apneas, each greater than 10 seconds in duration, per hour of sleep; and one or more of the following: frequent arousals from sleep associated with the apneas, bradytachycardia, or arterial oxygen desaturation in association with the apneas. In addition, for entry into these studies, all patients were required to have excessive sleepiness as demonstrated by a score ≥10 on the Epworth Sleepiness Scale (ESS), despite treatment with continuous positive airway pressure (CPAP). Evidence that CPAP was effective in reducing episodes of apnea/hypopnea was required along with documentation of CPAP use.

Patients were required to be compliant with CPAP, defined as CPAP use ≥4 hours/night on ≥70% of nights. CPAP use continued throughout the study. In both studies, the primary measures of effectiveness were 1) sleep latency, as assessed by the Maintenance of Wakefulness Test (MWT) and 2) the change in the patient’s overall disease status, as measured by the Clinical Global Impression of Change (CGI-C) at the final visit. For a successful trial both measures had to show statistically significant improvement.

The MWT measures latency (in minutes) to sleep onset. An extended MWT was performed with test sessions at 2 hour intervals between 9AM and 7PM. The primary analysis was the average of the sleep latencies from the first four test sessions (9AM to 3PM). For each test session, the subject was asked to attempt to remain awake without using extraordinary measures. Each test session was terminated after 30 minutes if no sleep occurred or immediately after sleep onset. The CGI-C is a 7-point scale, centered at No Change, and ranging from Very Much Worseto Very Much Improved. Evaluators were not given any specific guidance about the criteria they were to apply when rating patients.

In the first study, a total of 395 patients with OSA were randomized to receive NUVIGIL 150 mg/day, NUVIGIL 250 mg/day or matching placebo. Patients treated with NUVIGIL showed a statistically significant improvement in the ability to remain awake compared to placebo-treated patients as measured by the MWT at final visit. A statistically significant greater number of patients treated with NUVIGIL showed improvement in overall clinical condition as rated by the CGI-C scale at final visit. The average sleep latencies (in minutes) in the MWT at baseline for the trials are shown in Table 3 below, along with the average change from baseline on the MWT at final visit. The percentages of patients who showed any degree of improvement on the CGI-C in the clinical trials are shown in Table 4 below. The two doses of NUVIGIL produced statistically significant effects of similar magnitudes on the MWT, and also on the CGI-C.

In the second study, 263 patients with OSA were randomized to either NUVIGIL 150 mg/day or placebo. Patients treated with NUVIGIL showed a statistically significant improvement in the ability to remain awake compared to placebo-treated patients as measured by the MWT (Table 3). A statistically significant greater number of patients treated with NUVIGIL showed improvement in overall clinical condition as rated by the CGI-C scale (Table 4).

Nighttime sleep measured with polysomnography was not affected by the use of NUVIGIL in either study.

14.2 Narcolepsy

The effectiveness of NUVIGIL in improving wakefulness in patients with excessive sleepiness associated with narcolepsy was established in one 12-week, multi-center, placebo-controlled, parallel-group, double-blind study of outpatients who met the criteria for narcolepsy. A total of 196 patients were randomized to receive NUVIGIL 150 or 250 mg/day, or matching placebo. The criteria for narcolepsy include either: 1) recurrent daytime naps or lapses into sleep that occur almost daily for at least three months, plus sudden bilateral loss of postural muscle tone in association with intense emotion (cataplexy); or 2) a complaint of excessive sleepiness or sudden muscle weakness with associated features: sleep paralysis, hypnagogic hallucinations, automatic behaviors, disrupted major sleep episode; and polysomnography demonstrating one of the following: sleep latency less than 10 minutes or rapid eye movement (REM) sleep latency less than 20 minutes and a Multiple Sleep Latency Test (MSLT) that demonstrates a mean sleep latency of less than 5 minutes and two or more sleep onset REM periods and no medical or mental disorder accounts for the symptoms. For entry into these studies, all patients were required to have objectively documented excessive daytime sleepiness, via MSLT with a sleep latency of 6 minutes or less and the absence of any other clinically significant active medical or psychiatric disorder. The MSLT, an objective polysomnographic assessment of the patient’s ability to fall asleep in an unstimulating environment, measured latency (in minutes) to sleep onset averaged over 4 test sessions at 2-hour intervals. For each test session, the subject was told to lie quietly and attempt to sleep. Each test session was terminated after 20 minutes if no sleep occurred or immediately after sleep onset.

The primary measures of effectiveness were: 1) sleep latency as assessed by the Maintenance of Wakefulness Test (MWT); and 2) the change in the patient’s overall disease status, as measured by the CGI-C at the final visit [see Clinical Studies (14.1)for a description of these measures ]. Each MWT test session was terminated after 20 minutes if no sleep occurred or immediately after sleep onset in this study.

Patients treated with NUVIGIL showed a statistically significantly enhanced ability to remain awake on the MWT at each dose compared to placebo at final visit [ Table 3]. A statistically significant greater number of patients treated with NUVIGIL at each dose showed improvement in overall clinical condition as rated by the CGI-C scale at final visit [ Table 4].

The two doses of NUVIGIL produced statistically significant effects of similar magnitudes on the CGI-C. Although a statistically significant effect on the MWT was observed for each dose, the magnitude of effect was observed to be greater for the higher dose.

Nighttime sleep measured with polysomnography was not affected by the use of NUVIGIL.

14.3 Shift Work Disorder (SWD)

The effectiveness of NUVIGIL in improving wakefulness in patients with excessive sleepiness associated with SWD was demonstrated in a 12-week, multi-center, double-blind, placebo-controlled, parallel-group clinical trial. A total of 254 patients with chronic SWD were randomized to receive NUVIGIL 150 mg/day or placebo. All patients met the criteria for chronic SWD. The criteria include: 1) either, a) a primary complaint of excessive sleepiness or insomnia which is temporally associated with a work period (usually night work) that occurs during the habitual sleep phase, or b) polysomnography and the MSLT demonstrate loss of a normal sleep-wake pattern (i.e., disturbed chronobiological rhythmicity); and 2) no other medical or mental disorder accounts for the symptoms; and 3) the symptoms do not meet criteria for any other sleep disorder producing insomnia or excessive sleepiness (e.g., time zone change [jet lag] syndrome).

It should be noted that not all patients with a complaint of sleepiness who are also engaged in shift work meet the criteria for the diagnosis of SWD. In the clinical trial, only patients who were symptomatic for at least 3 months were enrolled.

Enrolled patients were also required to work a minimum of 5 night shifts per month, have excessive sleepiness at the time of their night shifts (MSLT score ≤6 minutes), and have daytime insomnia documented by a daytime polysomnogram.

The primary measures of effectiveness were: 1) sleep latency, as assessed by the Multiple Sleep Latency Test (MSLT) performed during a simulated night shift at the final visit; and 2) the change in the patient’s overall disease status, as measured by the CGI-C at the final visit [see Clinical Studies (14.1)for a description of these measures ].

Patients treated with NUVIGIL showed a statistically significant prolongation in the time to sleep onset compared to placebo-treated patients, as measured by the nighttime MSLT at final visit (Table 3). A statistically significant greater number of patients treated with NUVIGIL showed improvement in overall clinical condition as rated by the CGI-C scale at final visit (Table 4).

Daytime sleep measured with polysomnography was not affected by the use of NUVIGIL.

Table 3: Average Baseline Sleep Latency and Change from Baseline at Final Visit (MWT and MSLT in minutes)
Disorder | Measure | NUVIGIL; 150 mg* |  | NUVIGIL; 250 mg* |  | Placebo
 |  | Baseline | Change from Baseline | Baseline | Change from Baseline | Baseline | Change from Baseline
OSA I | MWT | 21.5 | 1.7 | 23.3 | 2.2 | 23.2 | -1.7
OSA II | MWT | 23.7 | 2.3 | - | - | 23.3 | -1.3
Narcolepsy | MWT | 12.1 | 1.3 | 9.5 | 2.6 | 12.5 | -1.9
SWD | MSLT | 2.3 | 3.1 | - | - | 2.4 | 0.4
*Significantly different than placebo for all trials (p<0.05)

Table 4: Clinical Global Impression of Change (CGI-C) (Percent of Patients Who Improved at Final Visit)
Disorder | NUVIGIL; 150 mg* | NUVIGIL; 250 mg* | Placebo
OSA I | 71% | 74% | 37%
OSA II | 71% | - | 53%
Narcolepsy | 69% | 73% | 33%
SWD | 79% | - | 59%
*Significantly different than placebo for all trials (p<0.05)

16 HOW SUPPLIED/STORAGE AND HANDLING

16.1 How Supplied

NUVIGIL®(armodafinil) Tablets are available as follows:

50 mg: Each round, white to off-white tablet is debossed with on one side and "205" on the other.
NDC 60429-001-30 – Bottles of 30

150 mg: Each oval, white to off-white tablet is debossed with on one side and "215" on the other.
NDC 60429-002-30 – Bottles of 30

200 mg: Each rounded, rectangular, white to off-white tablet is debossed with on one side and "220" on the other.
NDC 60429-003-30 – Bottles of 30

250 mg: Each oval, white to off-white tablet is debossed with on one side and "225" on the other.
NDC 60429-004-30 – Bottles of 30

16.2 Storage

Store at 20oC - 25oC (68oF - 77oF).

17 PATIENT COUNSELING INFORMATION

Advise the patient to read the FDA-approved patient labeling (Medication Guide).

Serious Dermatologic Reactions

Advise patients and caregivers about the risk of potentially fatal serious skin reactions. Educate patients about the signs and symptoms that may signal a serious skin reaction. Instruct patients to discontinue NUVIGIL and consult with their healthcare provider immediately if a skin reaction such as rash, mouth sores, blisters, or peeling skin occurs during treatment with NUVIGIL [see Warnings and Precautions (5.1)].

DRESS/Multi-organ Hypersensitivity

Instruct patients that a fever associated with signs of other organ system involvement (e.g., rash, lymphadenopathy, hepatic dysfunction) may be drug-related and should be reported to their healthcare provider immediately [see Warnings and Precautions (5.2)].

Angioedema and Anaphylactic Reactions

Advise patients of life-threatening symptoms suggesting anaphylaxis or angioedema (such as hives, difficulty in swallowing or breathing, hoarseness, or swelling of the face, eyes, lips, or tongue) that can occur with NUVIGIL. Instruct them to discontinue NUVIGIL and immediately report these symptoms to their healthcare provider [see Warnings and Precautions (5.3)].

Wakefulness

Advise patients that treatment with NUVIGIL will not eliminate their abnormal tendency to fall asleep. Advise patients that they should not alter their previous behavior with regard to potentially dangerous activities (e.g., driving, operating machinery) or other activities requiring appropriate levels of wakefulness, until and unless treatment with NUVIGIL has been shown to produce levels of wakefulness that permit such activities. Advise patients that NUVIGIL is not a replacement for sleep.

Continuing Previously Prescribed Treatments

Inform patients that it may be critical that they continue to take their previously prescribed treatments (e.g., patients with OSA receiving CPAP should continue to do so).

Psychiatric Symptoms

Advise patients to stop taking NUVIGIL and contact their physician right away if they experience, depression, anxiety, or signs of psychosis or mania.

Pregnancy

Advise women that there is a pregnancy exposure registry that monitors pregnancy outcomes in women exposed to NUVIGIL during pregnancy [see Use in Specific Populations (8.1)].

Females of Reproductive Potential

Caution females regarding the potential increased risk of pregnancy when using hormonal contraceptives (including depot or implantable contraceptives) with NUVIGIL and advise females who are using a hormonal method of contraception to use an additional barrier method or an alternative non-hormonal method of contraception during treatment with NUVIGIL and for one month after discontinuation of NUVIGIL.

Concomitant Medication

Advise patients to inform their physician if they are taking, or plan to take, any prescription or over‑the‑counter drugs, because of the potential for interactions between NUVIGIL and other drugs.

Alcohol

Advise patients that the use of NUVIGIL in combination with alcohol has not been studied. Advise patients that it is prudent to avoid alcohol while taking NUVIGIL.

Dispense with Medication Guide available at https://www.apotex.com/products/us/mg.asp.

Manufactured for:
Apotex Corp.
Weston, Florida

33326 USA

All rights reserved.

ApoPharma is a registered trademark of Apotex Inc.

Marketed by:
GSMS, Inc.
Camarillo, CA 93012 USA

MEDICATION GUIDE

NUVIGIL (nu-vij-el) (armodafinil) tablets, for oral use, C-IV

Medication Guide available at https://www.apotex.com/products/us/mg.asp

Read this Medication Guide before you start taking NUVIGIL and each time you get a refill. There may be new information. This information does not take the place of talking with your doctor about your medical condition or treatment.

What is the most important information I should know about NUVIGIL?

NUVIGIL is a federal controlled substance (C-IV) because it can be abused or lead to dependence. Keep NUVIGIL in a safe place to prevent misuse and abuse. Selling or giving away NUVIGIL may harm others, and is against the law.Tell your doctor if you have ever abused or been dependent on alcohol, prescription medicines or street drugs.

NUVIGIL may cause serious side effects including a serious rash or a serious allergic reaction that may affect parts of your body such as your liver or blood cells. Any of these may need to be treated in a hospital and may be life-threatening.

Stop taking NUVIGIL and call your doctor right away or get emergency help if you have any of these symptoms:

- skin rash, hives, sores in your mouth, or your skin blisters and peels
- swelling of your face, eyes, lips, tongue, or throat
- trouble swallowing, breathing, or hoarseness
- fever, shortness of breath, swelling of the legs, yellowing of the skin or whites of theeyes, or dark urine.

If you have a severe rash with NUVIGIL, stopping the medicine may not keep the rash from becoming life-threatening or causing you to be permanently disabled or disfigured.

NUVIGIL is not approved for use in children for any medical condition.

It is not known if NUVIGIL is safe and effective in children under the age of 18.

What is NUVIGIL?

NUVIGIL is a prescription medicine used to improve wakefulness in adults who are very sleepy due to one of the following diagnosed sleep disorders:

- narcolepsy
- obstructive sleep apnea (OSA). NUVIGIL is used with other medical treatments for this sleep disorder NUVIGIL does not take the place of using your CPAP machine or other treatments that your doctor has prescribed for this condition. It is important that you continue to use these treatments as prescribed by your doctor.
- shift work disorder (SWD)
  NUVIGIL will not cure these sleep disorders. NUVIGIL may help the sleepiness caused by these conditions, but it may not stop all your sleepiness. NUVIGIL does not take the place of getting enough sleep. Follow your doctor's advice about good sleep habits and using other treatments.

Do not take NUVIGIL:

- are allergic to any of its ingredients. See the end of this Medication Guide for a complete list of ingredients in NUVIGIL.
- have had a rash or allergic reaction to either armodafinil (NUVIGIL) or modafinil (PROVIGIL®). These medicines are very similar.

Before you take NUVIGIL, tell your doctor about all of your medical conditions, including if you:

- have a history of mental health problems, including psychosis
- have heart problems or had a heart attack
- have high blood pressure. Your blood pressure may need to be checked more often while taking NUVIGIL.
- have liver or kidney problemshave a history of drug or alcohol abuse or addiction
- are pregnant or planning to become pregnant. It is not known if NUVIGIL will harm your unborn baby.
  Pregnancy Registry: There is a registry for women who become pregnant during treatment with NUVIGIL. The purpose of this registry is to collect information about the safety of NUVIGIL during pregnancy. Contact the registry as soon as you learn that you are pregnant, or ask your doctor to contact the registry for you. You or your doctor can get information and enroll you in the registry by calling 1-866-404- 4106.
- are breastfeeding. It is not known if NUVIGIL passes into your milk. Talk to your doctor about the best way to feed your baby if you take NUVIGIL.

Tell your doctor about all the medicines you take, including prescription and over-the-counter medicines, vitamins, and herbal supplements. NUVIGIL and many other medicines can interact with each other, sometimes causing side effects. NUVIGIL may affect the way other medicines work, and other medicines may affect how NUVIGIL works. Your dose of NUVIGIL or certain other medicines may need to be changed. Especially, tell your doctor if you use or take:

- a hormonal birth control method, such as birth control pills, shots, implants, patches, vaginal rings, and intrauterine devices (IUDs). Hormonal birth control methods may not work while you take NUVIGIL. Women who use one of these methods of birth control may have a higher chance for getting pregnant while taking NUVIGIL, and for 1 month after stopping NUVIGIL. You should use effective birth control while taking NUVIGIL and for 1 month after your final dose. Talk to your doctor about birth control choices that are right for you while taking NUVIGIL.

Know the medicines you take. Keep a list of them and show it to your doctor and pharmacist when you get a new medicine. Your doctor or pharmacist will tell you if it is safe to take NUVIGIL and other medicines together. Do not start any new medicines with NUVIGIL unless your doctor has told you it is okay.

How should I take NUVIGIL?

- Take NUVIGIL exactly as prescribed by your doctor. Your doctor will prescribe the dose of NUVIGIL that is right for you. Do not change your dose of NUVIGIL without talking to your doctor.
- Your doctor will tell you the right time of day to take NUVIGIL.
  - People with narcolepsy or OSA usually take NUVIGIL one time each day in the morning.
  - People with SWD usually take NUVIGIL about 1 hour before their work shift.
- Do not change the time of day you take NUVIGIL unless you have talked to your doctor. If you take NUVIGIL too close to your bedtime, you may find it harder to go to sleep.
- You can take NUVIGIL with or without food.
- If you take more than your prescribed dose or if you take an overdose of NUVIGIL, call your doctor or poison control center right away.

Symptoms of an overdose of NUVIGIL may include:

- Trouble sleeping
- Confusion
- Feeling excited
- Nausea and diarrhea
- Chest pain
- Anxiety
- Restlessness
- Feeling disoriented
- Hearing, seeing, feeling, or sensing things that are not really there (hallucinations)
- A fast or slow heartbeat
- Increased blood pressure
- Shortness of breath

What should I avoid while taking NUVIGIL?

- Do not drive a car or do other dangerous activities until you know how NUVIGIL affects you. People with sleep disorders should always be careful about doing things that could be dangerous. Do not change your daily habits until your doctor tells you it is okay.
- You should avoid drinking alcohol. It is not known how drinking alcohol will affect you when taking NUVIGIL.

What are the possible side effects of NUVIGIL?

NUVIGIL may cause serious side effects.Stop taking NUVIGIL and call your doctor right away or get emergency help if you get any of the following:

- a serious rash or serious allergic reaction. (See “What is the most important information I should know about NUVIGIL?”)
- mental (psychiatric) symptoms, including:
  - depression
  - hearing, seeing, feeling, or sensing things that are not really there (hallucinations)
  - thoughts of suicide
  - other mental problems
  - feeling anxious
  - an extreme increase in activity and talking (mania)
  - aggressive behavior
- symptoms of a heart problem, including chest pain, abnormal heart beats, and trouble breathing.

The most common side effects of NUVIGIL include:

- headache
- dizziness
- nausea
- trouble sleeping

These are not all the possible side effects of NUVIGIL.

Call your doctor for medical advice about side effects. You may report side effects to FDA at 1-800-FDA-1088.

How should I store NUVIGIL?

- Store NUVIGIL at room temperature between 68°F to 77°F (20°C to 25°C).
- Keep NUVIGIL and all medicines out of the reach of children.

General information about the safe and effective use of NUVIGIL.

Medicines are sometimes prescribed for purposes other than those listed in a Medication Guide. Do not use NUVIGIL for a condition for which it was not prescribed. Do not give NUVIGIL to other people, even if they have the same symptoms that you have. It may harm them and is against the law. You can ask your pharmacist or healthcare provider for information about NUVIGIL that is written for health professionals.

What are the ingredients in NUVIGIL?

Active ingredient:armodafinil

Inactive ingredients:lactose monohydrate, microcrystalline cellulose, pregelatinized starch, croscarmellose sodium, povidone, and magnesium stearate.

Manufactured for:

Apotex Corp.

Weston, Florida

33326 USA

All rights reserved.

ApoPharma is a registered trademark of Apotex Inc.

For more information, go to www.apotex.comor call 1-800-706-5575

This Medication Guide has been approved by the U.S. Food and Drug Administration

Revised: February 2025

Marketed by:
GSMS, Inc.
Camarillo, CA 93012 USA

Package/Label Display Panel

NDC 60429-001-30
30 Tablets
NUVIGIL® (ARMODAFINIL) Tablets
50 mg CIV
Medication Guide Required: Each time NUVIGIL is dispensed, give the patient a Medication Guide.
Rx only

Package/Label Display Panel

NDC 60429-002-30
30 Tablets
NUVIGIL® (ARMODAFINIL) Tablets
150 mg CIV
Medication Guide Required: Each time NUVIGIL is dispensed, give the patient a Medication Guide.
Rx only

Package/Label Display Panel

NDC 60429-003-30
30 Tablets
NUVIGIL® (ARMODAFINIL) Tablets
200 mg CIV
Medication Guide Required: Each time NUVIGIL is dispensed, give the patient a Medication Guide.
Rx only

Package/Label Display Panel

NDC 60429-004-30
30 Tablets
NUVIGIL® (ARMODAFINIL) Tablets
250 mg CIV
Medication Guide Required: Each time NUVIGIL is dispensed, give the patient a Medication Guide.
Rx only